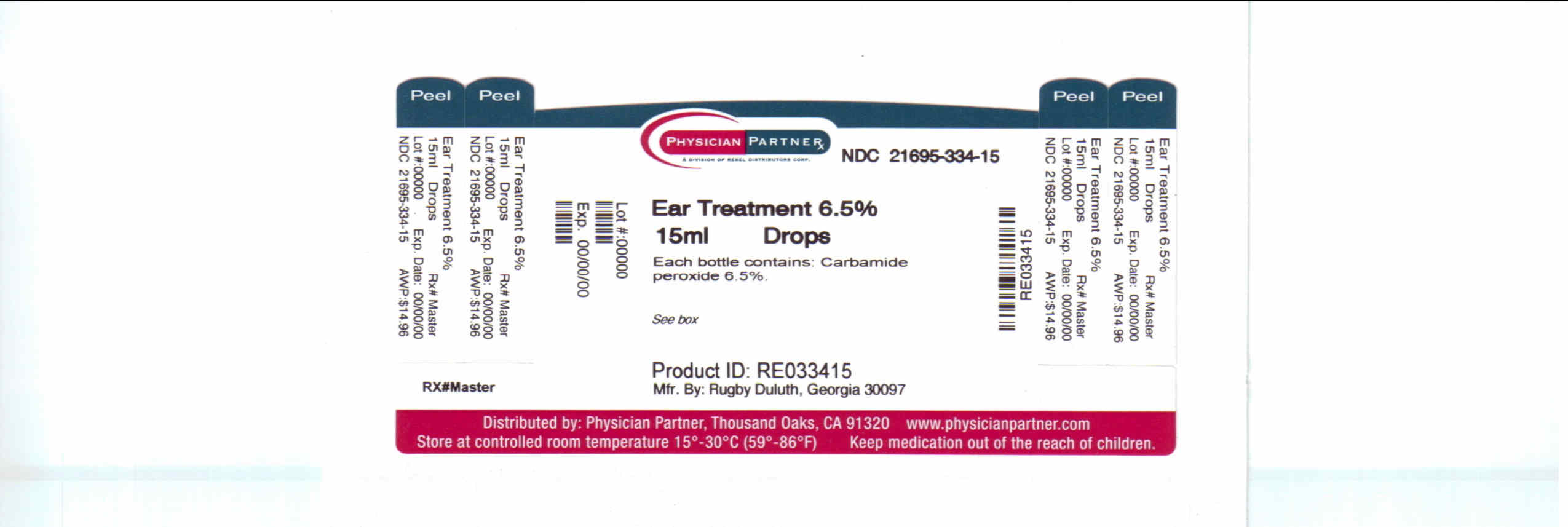 DRUG LABEL: Ear Wax Treatment
NDC: 21695-334 | Form: SOLUTION/ DROPS
Manufacturer: Rebel Distributors Corp
Category: otc | Type: HUMAN OTC DRUG LABEL
Date: 20110209

ACTIVE INGREDIENTS: Carbamide Peroxide 81.86 mg/1 mL
INACTIVE INGREDIENTS: Water; Citric Acid Monohydrate; Glycerin; Sodium Acid Pyrophosphate; Sodium Citrate; Propylene Glycol; Trolamine

Rugby®
Earwax
Treatment
Drops

Drug Facts

Active ingredient

Carbamide peroxide 6.5%

Purpose

Earwax removal aid

Use

softens, loosens and removes excessive earwax

Warnings

Do not use for more than 4 days

Ask a doctor before use if you have

- ear drainage or discharge
- ear pain, irritation, rash or are dizzy
- an injury or perforation (hole) of the eardrum or if you had ear surgery

When using this product avoid contact with the eyes

Stop use and ask a doctor if earwax remains longer than 4 days

Keep out of reach of children. If swallowed, get medical help or contact a Poison Control Center right away.

Directions

FOR USE IN THE EAR ONLY

adults and children over 12 years:

- tilt head sideways and place 5 to 10 drops into ear
- tip of applicator should not enter ear canal
- keep drops in ear for several minutes by tilting head or placing cotton in ear
- use twice daily for up to 4 days
- remove any wax remaining after treatment by gently flushing ear with warm water using a soft rubber bulb ear syringe

children under 12 years: ask a doctor

Other information

- store at room temperature 15° - 30°C (59° - 89°F)
- keep in a dry place

Inactive ingredients

citric acid (anhydrous), glycerin, propylene glycol, purified water, sodium acid pyrophosphate, sodium citrate (anhydrous), trolamine

Questions or comments?

Call 1-800-645-2158
9am - 5pm ET
Monday - Friday

Repackaged by:

Rebel Distributors Corp

Thousand Oaks, CA 91320

PRINCIPAL DISPLAY PANEL - 15 mL Carton

COMPARE TO
ACTIVE INGREDIENT IN
DEBROX®*

Rugby®
NDC 21695-334-15

Earwax
Treatment
Drops

Carbamide Peroxide 6.5 %

Helps Remove
Excessive Earwax

1/2 fl oz (15 mL)

SATISFACTION GUARANTEED
Rugby
OR YOUR MONEY BACK